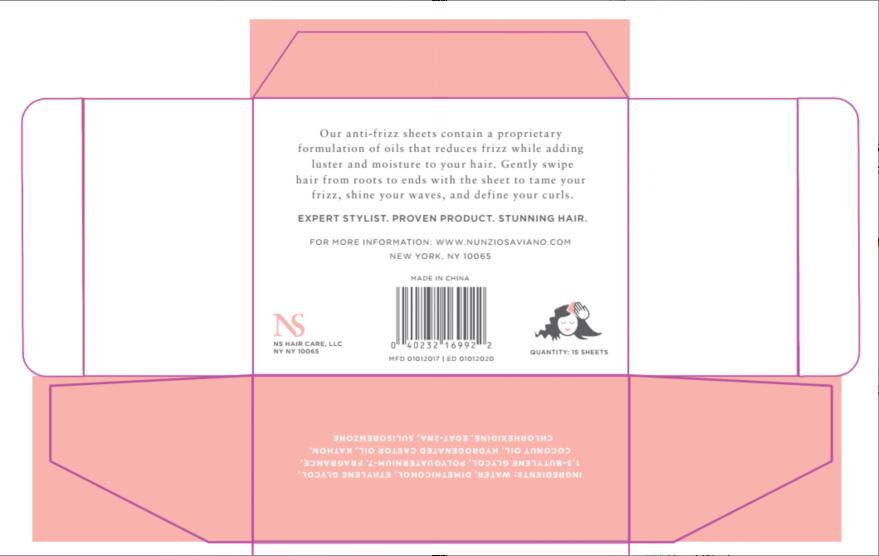 DRUG LABEL: anti-frizz sheets
NDC: 47993-240 | Form: SWAB
Manufacturer: NINGBO JIANGBEI OCEAN STAR TRADING CO.,LTD
Category: otc | Type: HUMAN OTC DRUG LABEL
Date: 20191022

ACTIVE INGREDIENTS: SULISOBENZONE 2 g/100 g
INACTIVE INGREDIENTS: WATER 89.49 g/100 g; DIMETHICONOL (50000 CST) 3 g/100 g; BUTYLENE GLYCOL 2 g/100 g; POLYQUATERNIUM-7 (70/30 ACRYLAMIDE/DADMAC; 900000 MW) 1 g/100 g; ETHYLENE GLYCOL 2 g/100 g; AROMADENDRIN 0.2 1/100 g; COCONUT OIL 0.1 1/100 g; HYDROGENATED COCONUT OIL 0.1 1/100 g; 5-CHLORO-2-METHYL-3-ISOTHIAZOLONE 1-OXIDE 0.08 1/100 g; CHLORHEXIDINE 0.02 1/100 g; EDETATE DISODIUM 0.01 1/100 g

Active Ingredients

Active ingredients--------------purpose

SULISOBENZONE-------2%

Uses:
Sunscreen and moisturizing. Recommended for repeated use.

Warnings:

For external use only.Avoid contact with eyes and keep out of reach of children.

Directions:

Tear open packet and remove sheet.Gently swipe hair from roots to ends with the sheet to tame your frizz,shine your waves,and define your curls.

KEEP OUT OF REACH OF CHILDREN

Children under 6 years of age should be super vised when using this product.

Inactive Ingredients:

Water,Dimethiconol,Ethylene Glycol,1,3-Butylene Glycol,Polyquaternium-7,Fragrance,Coconut Oil,Hydrogenated Castor Oil,Kathon,Chlorhexidine,EDTA-2NA